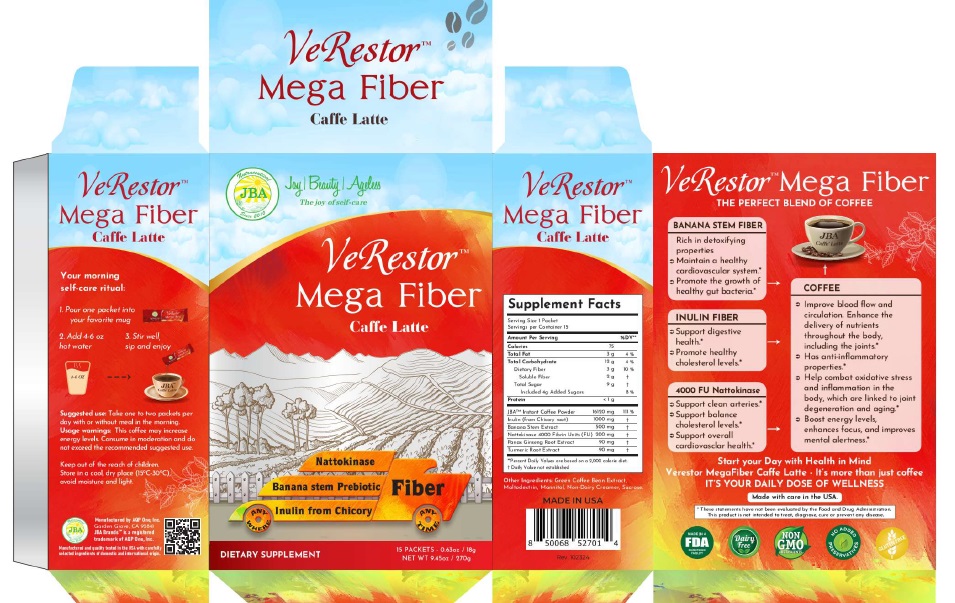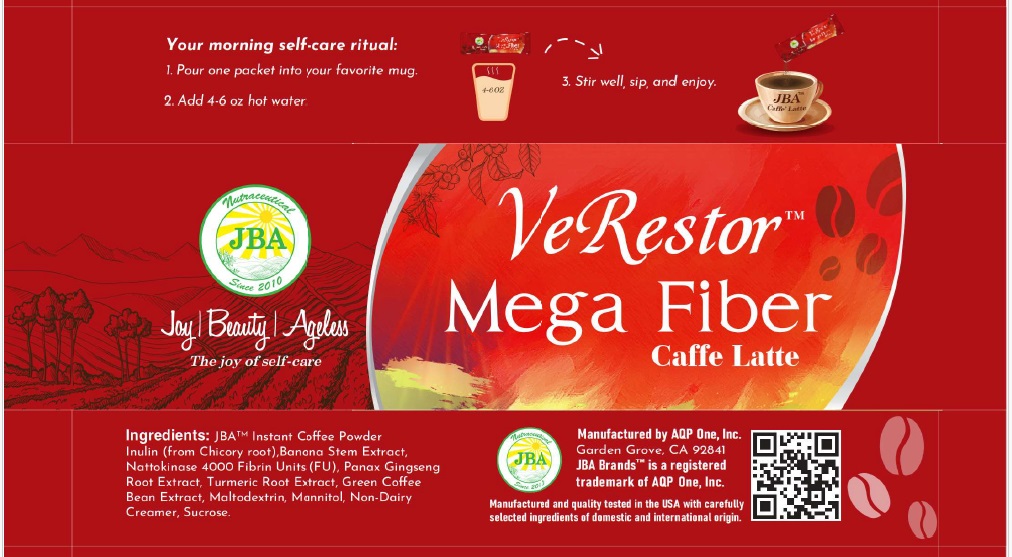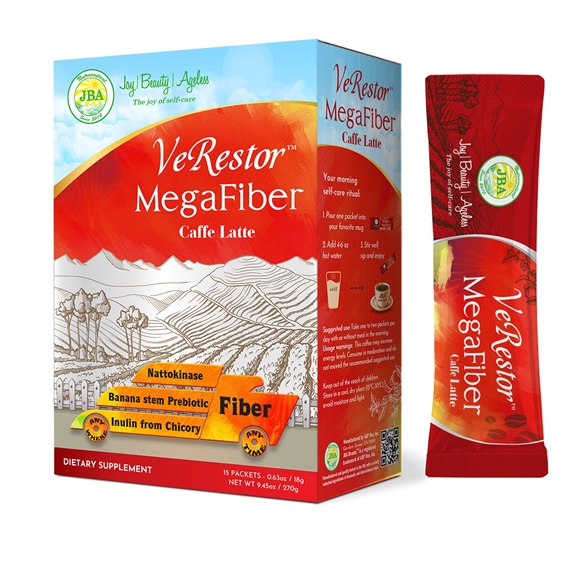 DRUG LABEL: JBA Verestor Mega Fiber Caffe Latte
NDC: 13411-863 | Form: POWDER
Manufacturer: Advanced Pharmaceutical Services, Inc. Dba Affordable Quality Pharmaceuticals
Category: otc | Type: HUMAN OTC DRUG LABEL
Date: 20251128

ACTIVE INGREDIENTS: INULIN 1000 mg/1 1; BANANA 500 mg/1 1; NATTOKINASE 200 mg/1 1; ASIAN GINSENG 90 mg/1 1; TURMERIC 90 mg/1 1
INACTIVE INGREDIENTS: COFFEE BEAN; MALTODEXTRIN; MANNITOL; SUCROSE

Identity

Dietary supplement

Direction

Take one or two packets per day with or without meal in the morning.

Safe handling warning

VERESTOR MEGA FIBER CAFFE LATTE
The Perfect Blend of Coffee and Fiber

Banana Stem Fiber
Rich in detoxifying properties
Maintain a healthy cardiovascular system*
Promote the growth of healthy gut bacteria.*

Inulin Fiber
Support digestive health.*
Promote healthy cholesterol levels.*

4000 FU Nattokinase
Support clean arteries.*
Support balance cholesterol levels.*
Support overall cardiovascular health.*

Coffee
Improve blood flow and circulation. Enhance the delivery of nutrient throughout the body including the joints.*
Has anti-inflammatory properties.*
Help combat oxidative stress and inflammation in the body, which are linked to joint degeneration and aging.*
Boost energy levels, enhance focus, and improve mental alertness.*

Start your Day with Health in Mind
VerestorTM Mega Fiber Caffe Latte – It’s more than just coffee
IT’S YOUR DAILY DOSE OF WELLNESS

* These statements have not been evaluated by the Food & Drug Administration. This product is not intended to diagnose, treat, cure, or prevent any disease.

PRECAUTIONS

This coffee may increase energy levels. Consume in moderation and do not exceed the recommended suggested use.

Keep Out of The Reach of Children. Store in a cool, dry place (59oF-86oF), avoid moisture and light.

WARNINGS

Other Ingredients

Green Coffee Bean Extract, Maltodextrin, Mannitol, Non-Dairy Creamer, Sucrose